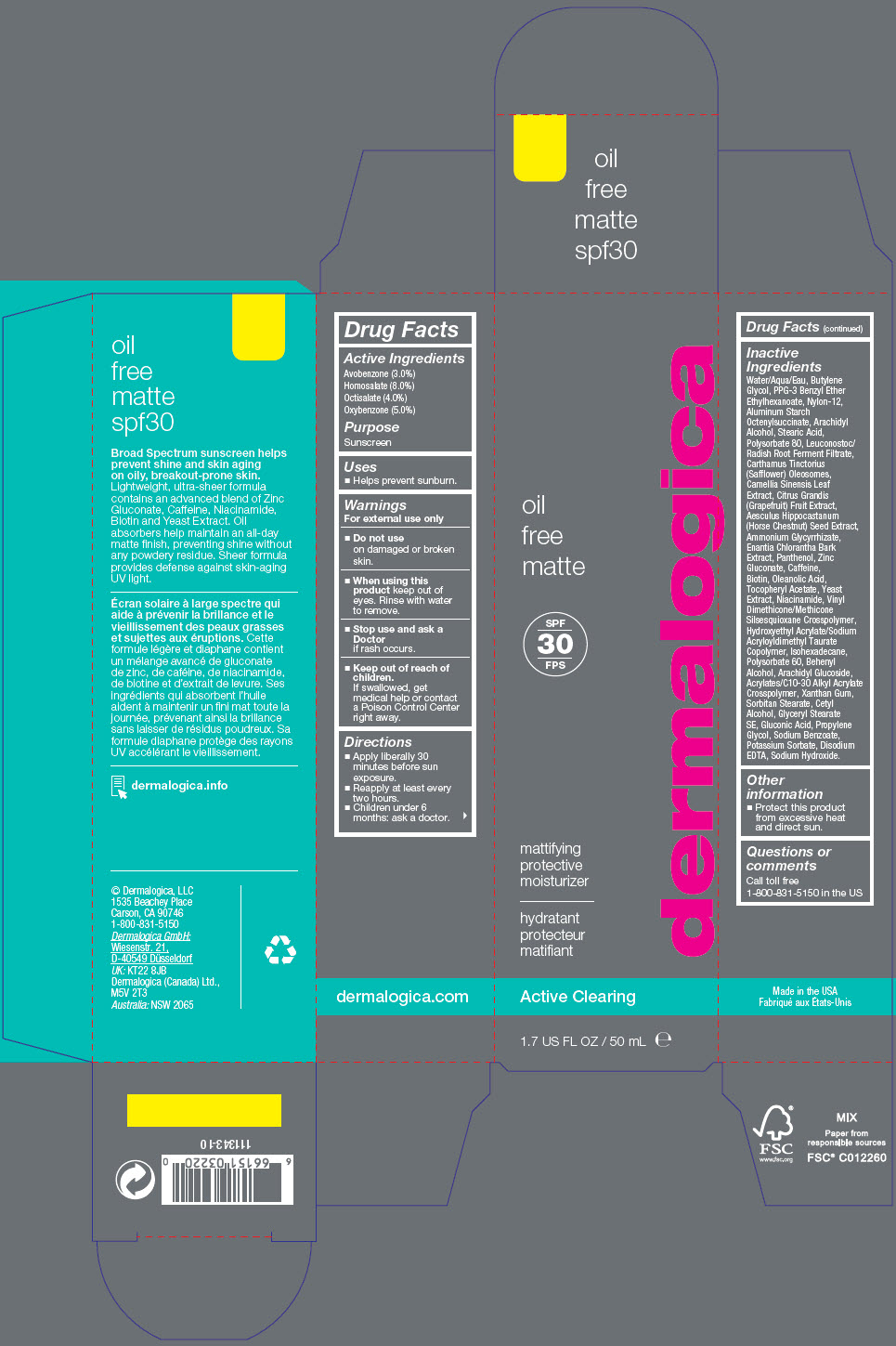 DRUG LABEL: Oil Free Matte 
NDC: 68479-110 | Form: LOTION
Manufacturer: Dermalogica
Category: otc | Type: HUMAN OTC DRUG LABEL
Date: 20221208

ACTIVE INGREDIENTS: Avobenzone 30 mg/1 mL; Homosalate 80 mg/1 mL; Octisalate 40 mg/1 mL; Oxybenzone 50 mg/1 mL
INACTIVE INGREDIENTS: Water; PPG-3 Benzyl Ether Ethylhexanoate; Butylene Glycol; Nylon-12; Aluminum Starch Octenylsuccinate; Arachidyl Alcohol; Leuconostoc/Radish Root Ferment Filtrate; Stearic Acid; Polysorbate 80; Annickia Chlorantha Bark; Oleanolic Acid; Niacinamide; Yeast, Unspecified; Horse Chestnut; Ammonium Glycyrrhizate; Panthenol; Zinc Gluconate; Gluconic Acid; Propylene Glycol; Caffeine; Biotin; Carthamus Tinctorius Seed Oleosomes; .Alpha.-Tocopherol Acetate; Arachidyl Glucoside; Cetyl Alcohol; Glyceryl Stearate SE; VINYL DIMETHICONE/METHICONE SILSESQUIOXANE CROSSPOLYMER; Sorbitan Monostearate; HYDROXYETHYL ACRYLATE/SODIUM ACRYLOYLDIMETHYL TAURATE COPOLYMER (100000 MPA.S AT 1.5%); Isohexadecane; PUMMELO; Polysorbate 60; GREEN TEA LEAF; Xanthan Gum; Sodium Benzoate; Potassium Sorbate; Sodium Hydroxide; Edetate Disodium; Docosanol

Oil Free Matte
SPF 30

Drug Facts

Active Ingredients

Avobenzone (3.0%)
Homosalate (8.0%)
Octisalate (4.0%)
Oxybenzone (5.0%)

Purpose

Sunscreen

Uses

- Helps prevent sunburn.

Warnings

For external use only

- Do not use on damaged or broken skin.

- When using this product keep out of eyes. Rinse with water to remove.

- Stop use and ask a Doctor if rash occurs.

- Keep out of reach of children. If swallowed, get medical help or contact a Poison Control Center right away.

Directions

- Apply liberally 30 minutes before sun exposure.
- Reapply at least every two hours.
- Children under 6 months: ask a doctor.

Inactive Ingredients

Water/Aqua/Eau, Butylene Glycol, PPG-3 Benzyl Ether Ethylhexanoate, Nylon-12, Aluminum Starch Octenylsuccinate, Arachidyl Alcohol, Stearic Acid, Polysorbate 80, Leuconostoc/Radish Root Ferment Filtrate, Carthamus Tinctorius (Safflower) Oleosomes, Camellia Sinensis Leaf Extract, Citrus Grandis (Grapefruit) Fruit Extract, Aesculus Hippocastanum (Horse Chestnut) Seed Extract, Ammonium Glycyrrhizate, Enantia Chlorantha Bark Extract, Panthenol, Zinc Gluconate, Caffeine, Biotin, Oleanolic Acid, Tocopheryl Acetate, Yeast Extract, Niacinamide, Vinyl Dimethicone/Methicone Silsesquioxane Crosspolymer, Hydroxyethyl Acrylate/Sodium Acryloyldimethyl Taurate Copolymer, Isohexadecane, Polysorbate 60, Behenyl Alcohol, Arachidyl Glucoside, Acrylates/C10-30 Alkyl Acrylate Crosspolymer, Xanthan Gum, Sorbitan Stearate, Cetyl Alcohol, Glyceryl Stearate SE, Gluconic Acid, Propylene Glycol, Sodium Benzoate, Potassium Sorbate, Disodium EDTA, Sodium Hydroxide.

Other information

- Protect this product from excessive heat and direct sun.

Questions or comments

Call toll free 1-800-831-5150 in the US

PRINCIPAL DISPLAY PANEL - 50 mL Bottle Carton

dermalogica

oil
free
matte

SPF
30

mattifying
protective
moisturizer

Active Clearing

1.7 US FL OZ / 50 mL ℮